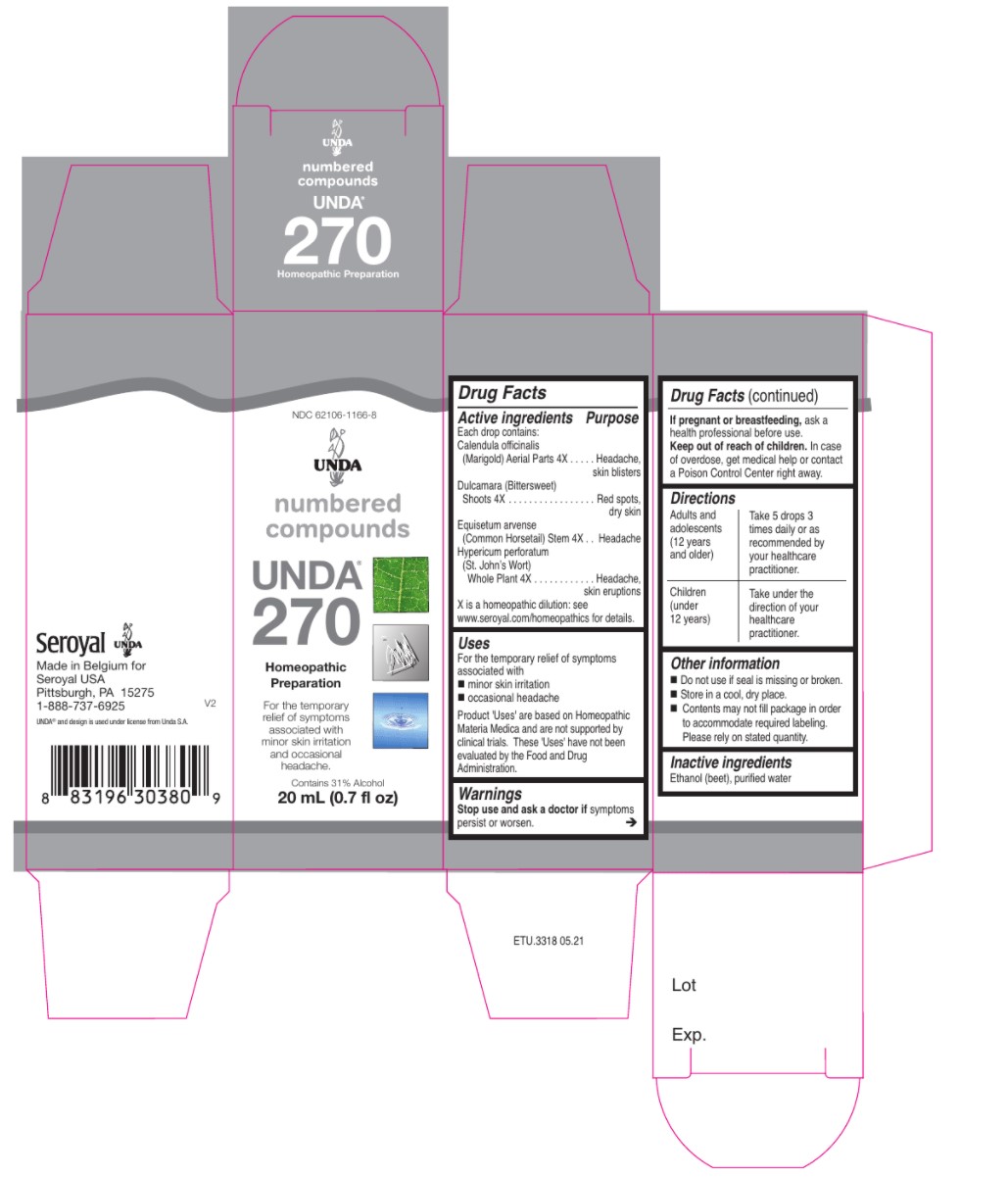 DRUG LABEL: UNDA 270
NDC: 62106-1166 | Form: LIQUID
Manufacturer: Seroyal USA
Category: homeopathic | Type: HUMAN OTC DRUG LABEL
Date: 20210715

ACTIVE INGREDIENTS: SOLANUM DULCAMARA STEM 4 [hp_X]/20 mL; CALENDULA OFFICINALIS FLOWERING TOP 4 [hp_X]/20 mL; EQUISETUM ARVENSE BRANCH 4 [hp_X]/20 mL; HYPERICUM PERFORATUM 4 [hp_X]/20 mL
INACTIVE INGREDIENTS: ALCOHOL; WATER

UNDA 270

Active ingredients
Each drop contains:
Calendula officinalis (Marigold) Aerial Parts 4X
Dulcamara (Bittersweet) Shoots 4X
Equisetum arvense (Common Horsetail) Stem 4X
Hypericum perforatum (St. John’s Wort) Whole Plant 4X

Uses
For the temporary relief of symptoms associated with
minor skin irritation
occasional headache

Warnings
Stop use and ask a doctor if symptoms persist or worsen.

If pregnant or breastfeeding, ask a health professional before use.
Keep out of reach of children. In case of overdose, get medical help or contact
a Poison Control Center right away.

Keep out of reach of children.

PREGNANCY OR BREAST FEEDING

If pregnant or breastfeeding, ask a health professional before use.

Other information
Do not use if seal is missing or broken.
Store in a cool, dry place.

Contents may not fill package in order
to accommodate required labeling.
Please rely on stated quantity.

Inactive ingredients
Ethanol (beet), purified water

Directions
Adults and adolescents (12 years and older)

Take 5 drops three times daily or as recommended by your healthcare practitioner.

Children (under 12 years)

Take under the direction of your healthcare practitioner.

Uses
For the temporary relief of symptoms associated with
minor skin irritation
occasional headache

Directions
Adults and adolescents (12 years and older)

Take 5 drops three times daily or as recommended by your healthcare practitioner.

Children (under 12 years)

Take under the direction of your healthcare practitioner.

PACKAGE LABEL

NDC 62106-1166-8

UNDA

numbered compounds

UNDA 270

Homeopathic Preparation

For the temporary relief of symptoms associated

with minor skin irritation and occasional headache.

Contains 31% Alcohol

0.7 fl oz (20 ml)